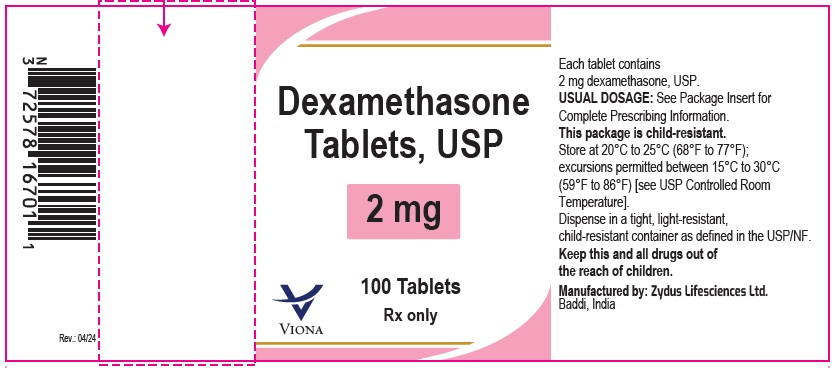 DRUG LABEL: Dexamethasone
NDC: 70771-1701 | Form: TABLET
Manufacturer: Zydus Lifesciences Limited
Category: prescription | Type: HUMAN PRESCRIPTION DRUG LABEL
Date: 20240330

ACTIVE INGREDIENTS: DEXAMETHASONE 2 mg/1 1
INACTIVE INGREDIENTS: LACTOSE MONOHYDRATE; MAGNESIUM STEARATE; STARCH, CORN; SUCROSE

Dexamethasone Tablets, USP

PACKAGE LABEL.PRINCIPAL DISPLAY PANEL

NDC 70771-1701-1

Dexamethasone Tablets, USP 2 mg

100 Tablets

Rx only

Zydus